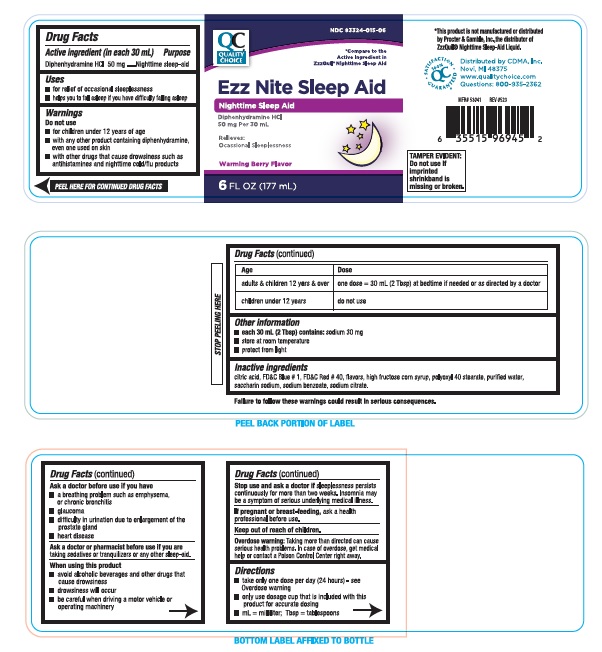 DRUG LABEL: Nighttime Sleep-Aid
NDC: 83324-015 | Form: LIQUID
Manufacturer: Chain Drug Marketing Association Inc.
Category: otc | Type: Human OTC Drug Label
Date: 20240319

ACTIVE INGREDIENTS: DIPHENHYDRAMINE HYDROCHLORIDE 50 mg/30 mL
INACTIVE INGREDIENTS: ANHYDROUS CITRIC ACID; FD&C BLUE NO. 1; FD&C RED NO. 40; HIGH FRUCTOSE CORN SYRUP; POLYOXYL 40 STEARATE; SACCHARIN SODIUM ANHYDROUS; SODIUM BENZOATE; SODIUM CITRATE

Quality Choice Nighttime Sleep Aid 633

ACTIVE INGREDIENT (in each 30mL)

Diphenhydramine HCl 50 mg

PURPOSE

Nighttime sleep-aid

USE(S)

- for relief of occasional sleeplessness
- helps you to fall asleep if you have difficulty falling asleep

WARNINGS

.

DO NOT USE

- for children under 12 years of age
- with any other product containing diphenhydramine, even one used on skin
- with other drugs that cause drowsiness such as antihistamines and nighttime cold/flu products

ASK A DOCTOR BEFORE USE IF YOU HAVE

- a breathing problem such as emphysema, or chronic bronchitis
- glaucoma
- difficulty in urination due to enlargement of the prostate gland
- heart disease

ASK A DOCTOR OR PHARMACIST BEFORE USE IF YOU ARE

taking sedatives or tranquilizers or any other sleep-aid.

WHEN USING THIS PRODUCT

- avoid alcoholic beverages and other drugs that cause drowsiness
- drowsiness will occur
- be careful when driving a motor vehicle or operating machinery

STOP USE AND ASK DOCTOR IF

sleepleness persists continuously for more than two weeks. Insomnia may be a symptom of serious underlying medical illness.

IF PREGNANT OR BREAST-FEEDING,

ask a health professional before use.

KEEP OUT OF REACH OF CHILDREN

.

OVERDOSE WARNING

Taking more than directed can cause serious health problems. In case of overdose, get medical help or contact a Poison Control Center right away.

DIRECTIONS

- take only one dose per day (24 hours) - see Overdose warning
- only use dosage cup that is included with this product for accurate dosing
- mL = millilitere; Tbsp = teblespoons

Age | Dose
adults & chlidren 12 year & over | one = 30 mL (2Tbsp) at bedtime if needed or as directed by a doctor
childrens under 12 years | do not use

OTHER INFORMATION

- each 30 mL (2 Tbsp) contain: sodium 30 mg
- store at room temperature
- protect from light

INACTIVE INGREDIENTS

citric acid, FD&C Blue # 1, FD&C Red # 40, flavors, high fructose corn syrup, polyoxyl 40 stearate, purified water, saccharine sodium, sodium benzoate, sodium citrate.

PRINCIPAL DISPLAY PANEL

NDC 83324-015-06

QC® QUALITY CHOICE

*Compare to the Active ingredient in ZzzQUIL® Nighttime Sleep Aid

Ezz Nite Sleep Aid

Nighttime Sleep-Aid

Diphenhydramine HCl

50 mg Per 30 mL

Relieves:

Occasional Sleeplessness

Warming Berry Flavor

6 FL OZ (177 ML)